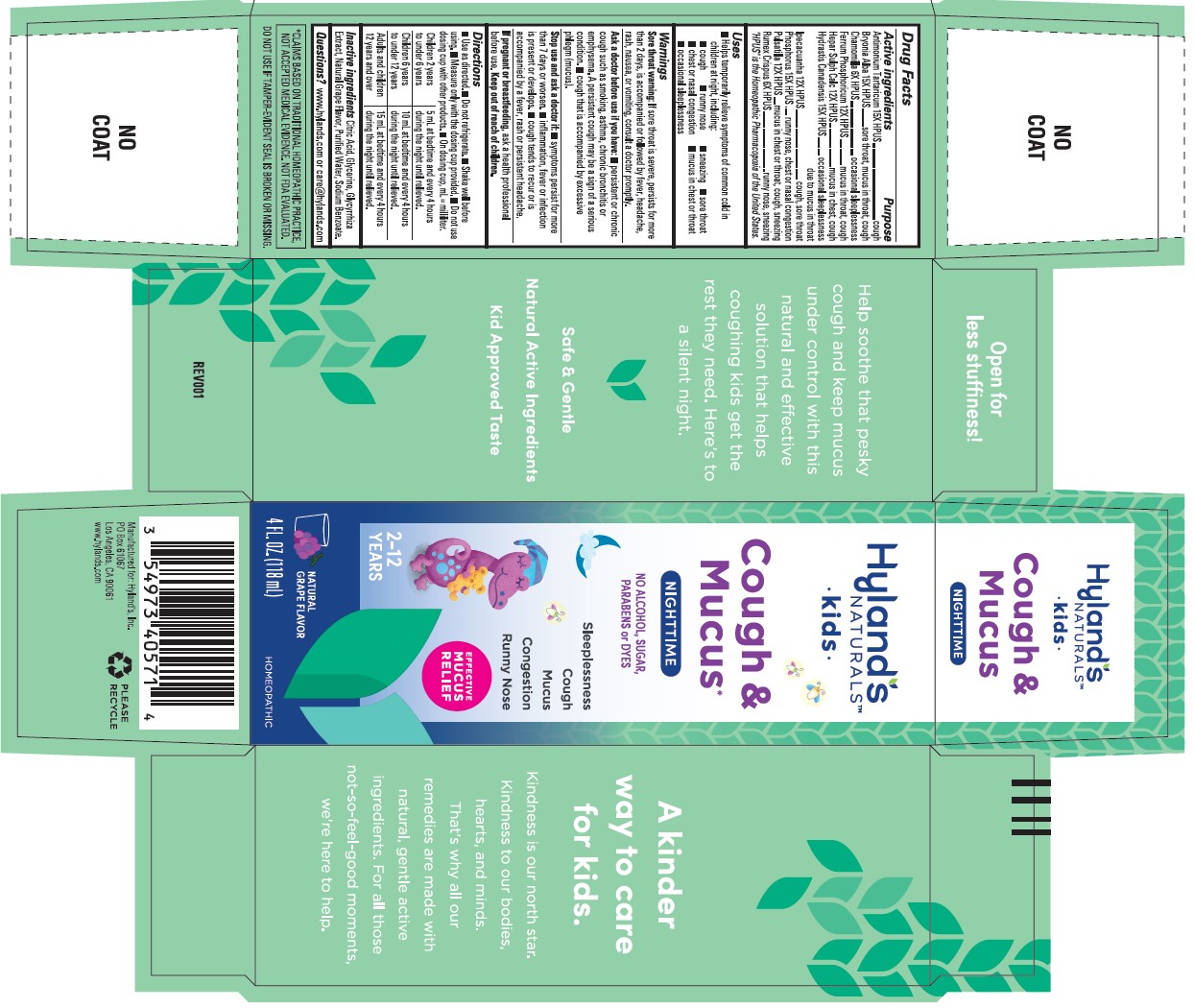 DRUG LABEL: Kids Cough and Mucus Nighttime Grape Flavor
NDC: 54973-4057 | Form: LIQUID
Manufacturer: Hyland's Consumer Health Inc.
Category: homeopathic | Type: HUMAN OTC DRUG LABEL
Date: 20260219

ACTIVE INGREDIENTS: RUMEX CRISPUS ROOT 6 [hp_X]/1 mL; IPECAC 12 [hp_X]/1 mL; ANTIMONY POTASSIUM TARTRATE 15 [hp_X]/1 mL; BRYONIA ALBA ROOT 15 [hp_X]/1 mL; MATRICARIA CHAMOMILLA WHOLE 6 [hp_X]/1 mL; FERROSOFERRIC PHOSPHATE 12 [hp_X]/1 mL; CALCIUM SULFIDE 12 [hp_X]/1 mL; PULSATILLA VULGARIS 12 [hp_X]/1 mL; GOLDENSEAL 15 [hp_X]/1 mL; PHOSPHORUS 15 [hp_X]/1 mL
INACTIVE INGREDIENTS: WATER; SODIUM BENZOATE; GLYCYRRHIZA GLABRA; CITRIC ACID MONOHYDRATE; GLYCERIN

Kids Cough & Mucus Nighttime Grape Flavor

PURPOSE

Temporarily relieves symptoms of common cold in children at night, including cough, runny nose, sneezing, sore throat, chest or nasal congestion, mucus in chest or throat, occasional sleeplessness

Drug Facts

Active ingredients

Active ingredients | Purpose
Antimonium Tartaricum 15X HPUS | cough
Bryonia Alba 15X HPUS | sore throat, mucus in throat, cough
Chamomilla 6X HPUS | occasional sleeplessness
Ferrum Phosphoricum 12X HPUS | mucus in throat, cough
Hepar Sulph Calc 12X HPUS | mucus in chest, cough
Hydrastis Canadensis 15X HPUS | occasional sleeplessness due to mucus in throat
Ipecacuanha 12X HPUS | cough, sore throat
Phosphorus 15X HPUS | runny nose, chest or nasal congestion
Pulsatilla 12X HPUS | mucus in chest or throat, cough, sneezing
Rumex Crispus 6X HPUS | runny nose, sneezing

"HPUS" is the Homeopathic Pharmacopoeia of the United States.

Uses

Temporarily relieves symptoms of common cold in children at night, including: ■ cough ■ runny nose ■ sneezing ■ sore throat
■ chest or nasal congestion ■ mucus in chest or throat ■ occasional sleeplessness

Warnings

Sore throat warning

If sore throat is severe, persists for more than 2 days, is accompanied or followed by fever, headache, rash, nausea, or vomiting, consult a doctor promptly.

Ask a doctor before use if you have

■ persistent or chronic cough such as smoking, asthma, chronic bronchitis or emphysema. A persistent cough may be a sign of a serious condition. ■ cough that is accompanied by excessive phlegm (mucus).

Stop use and ask a doctor if

■ symptoms persist for more than 7 days or worsen. ■ inflammation, fever or infection is present or develops. ■ cough tends to recur or is accompanied by a fever, rash or persistent headache.

If pregnant or breastfeeding

ask a health professional before use.

Directions

■ Use as directed. ■ Do not refrigerate. ■ Shake well before using. ■ Measure only with the dosing cup provided. ■ Do not use
dosing cup with other products. ■ On dosing cup, mL = milliliter.

Children 2 years to under 6 years | 5 mL at bedtime and every 4 hours during the night until relieved.
Children 6 years to under 12 years | 10 mL at bedtime and every 4 hours during the night until relieved.
Adults and children 12 years and over | 15 mL at bedtime and every 4 hours during the night until relieved.

Inactive ingredients

Citric Acid, Glycerine, Glycyrrhiza Extract, Natural Grape Flavor, Purified Water, Sodium Benzoate.

Questions?

www.hylands.com or care@hylands.com

Principal Display Panel

Hyland's

NATURALS™

•Kids•

Cough &

Mucus*

NIGHTTIME

NO ALCOHOL, SUGAR,

PARABENS or DYES

Sleeplessness

Cough

Mucus

Congestion

Runny Nose

EFFECTIVE

MUCUS

RELIEF

2-12

YEARS

NATURAL

GRAPE FLAVOR

4 FL. OZ. (118 mL)

HOMEOPATHIC